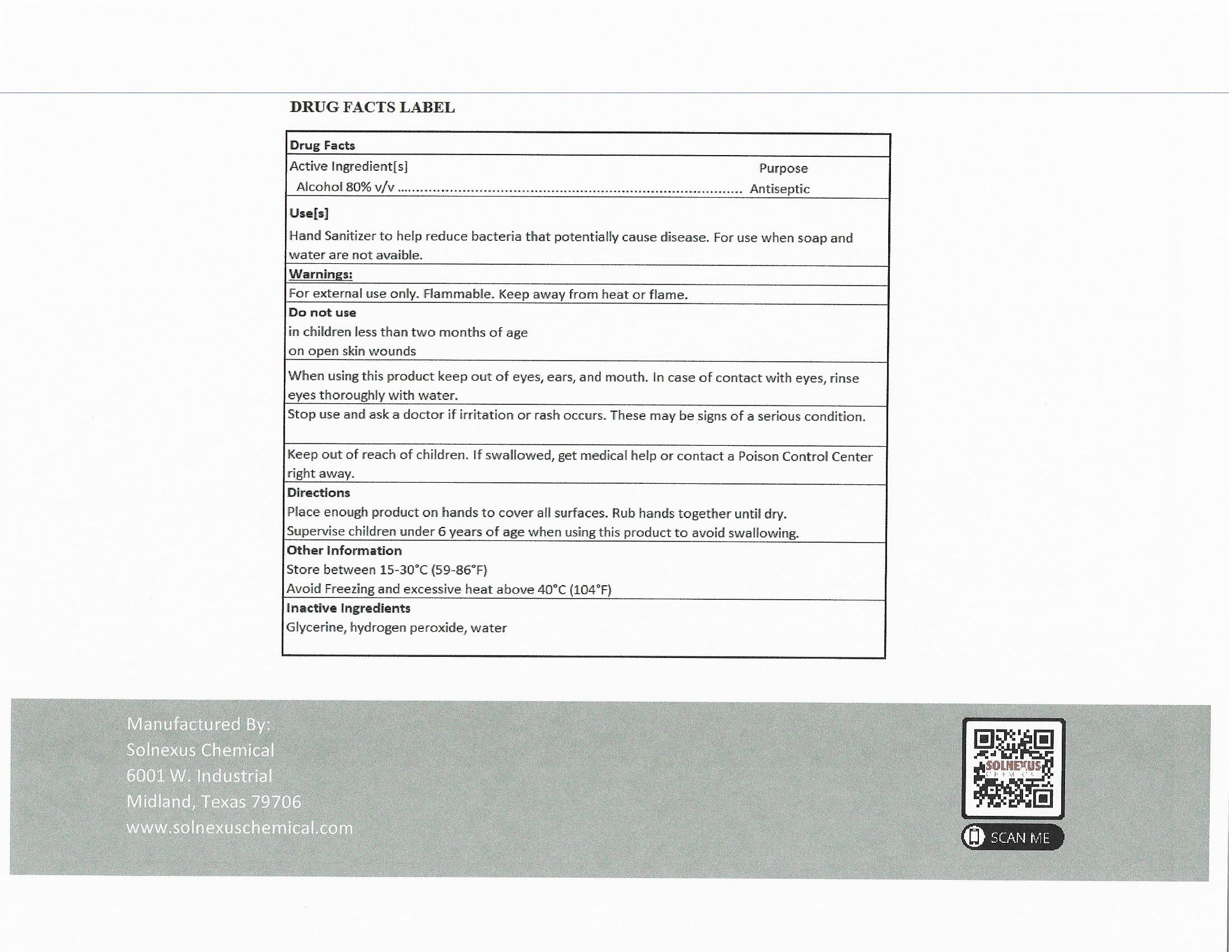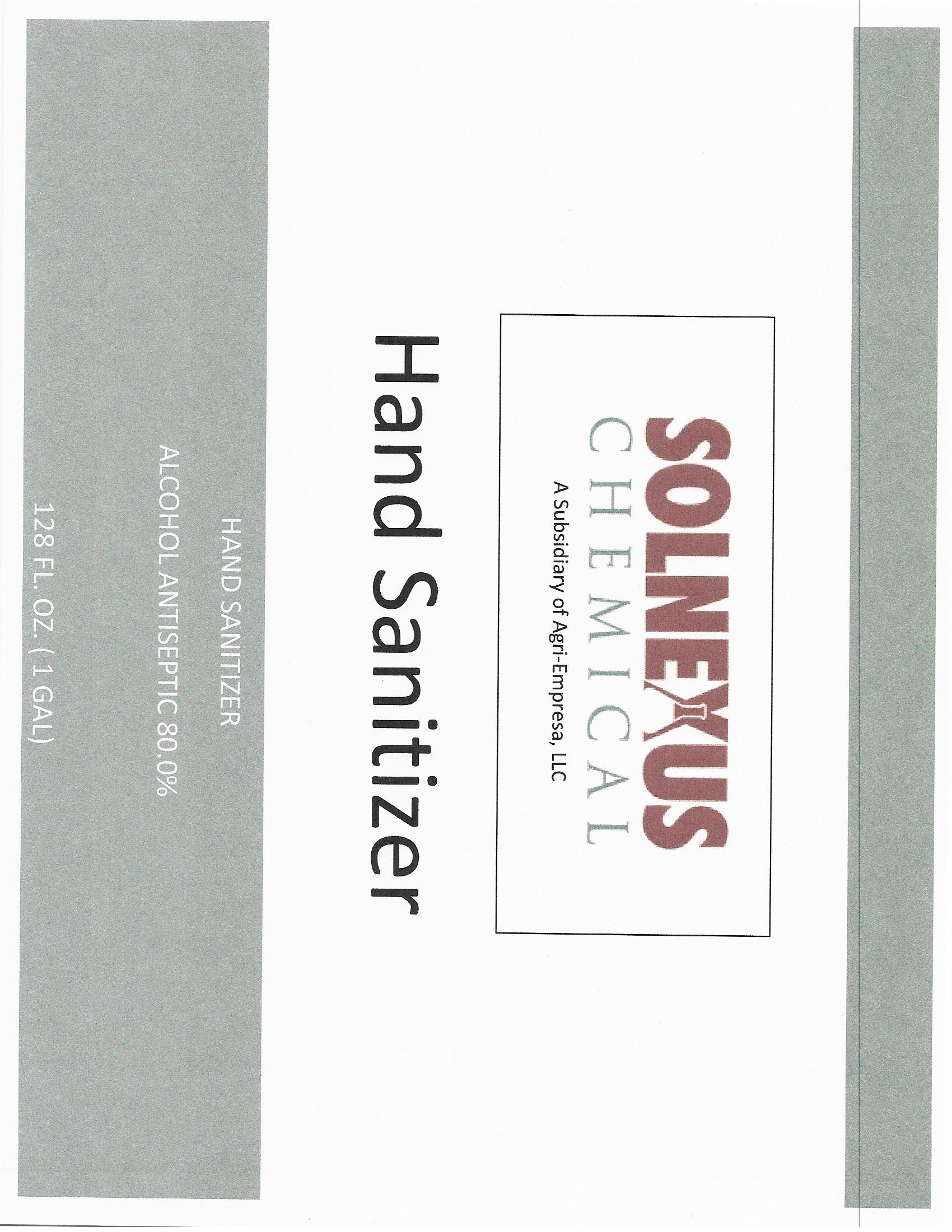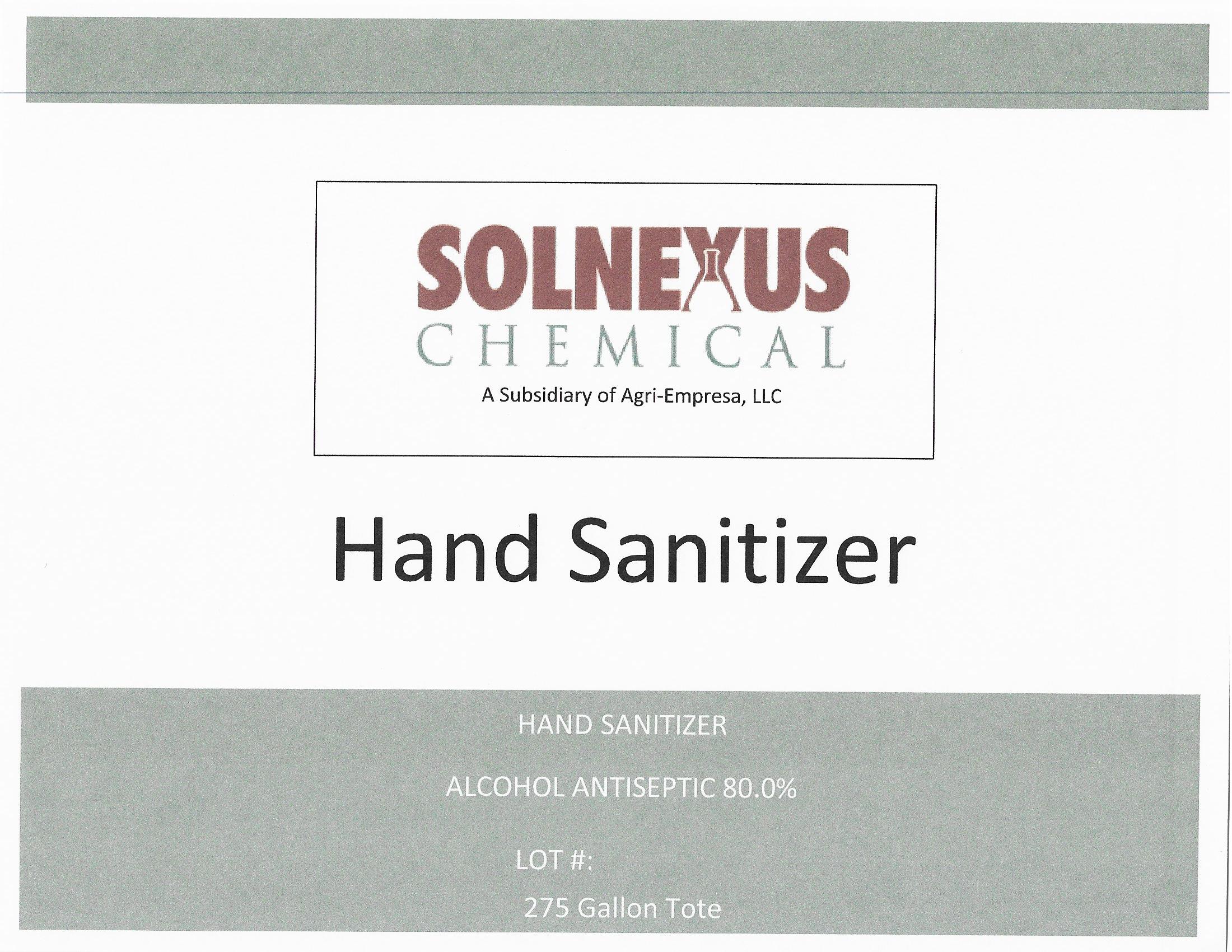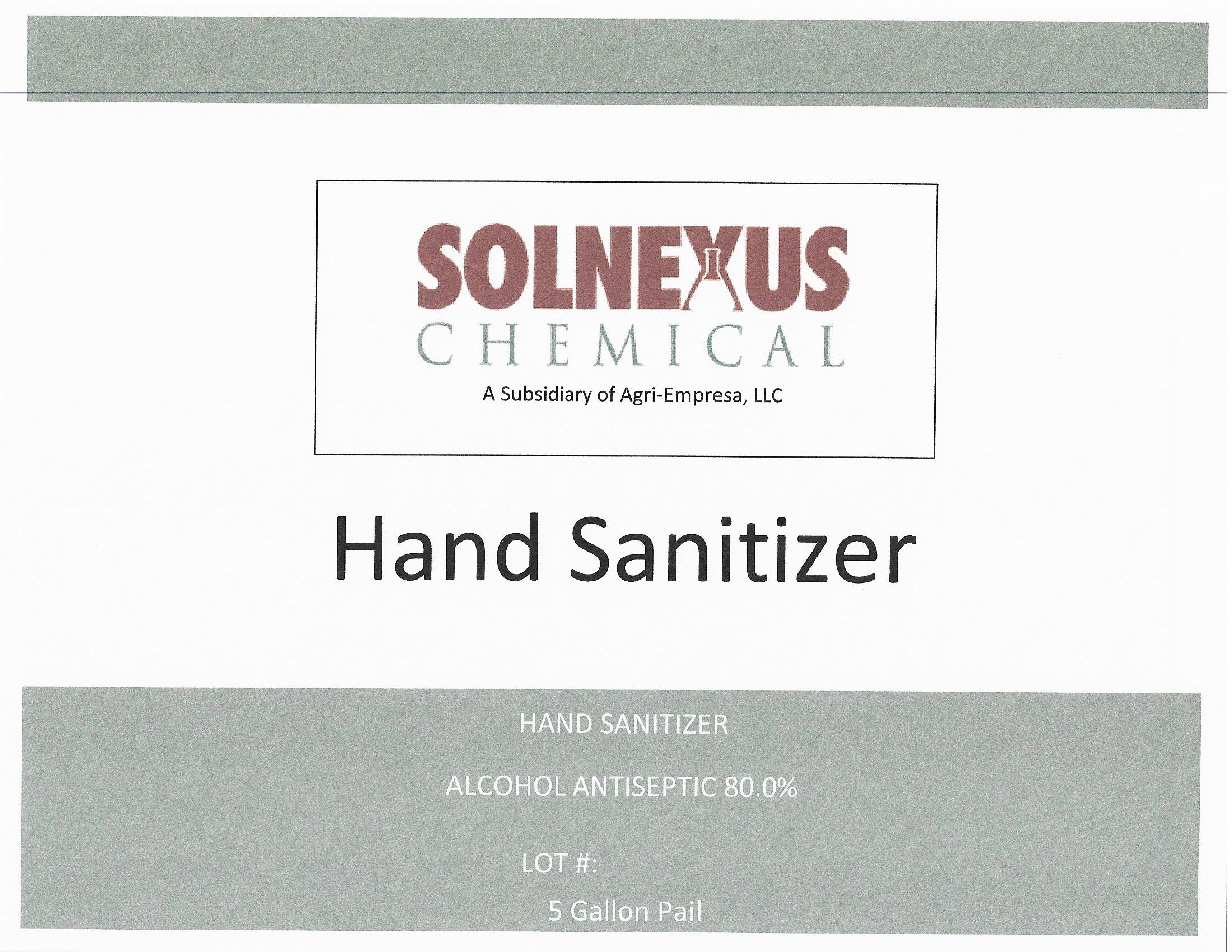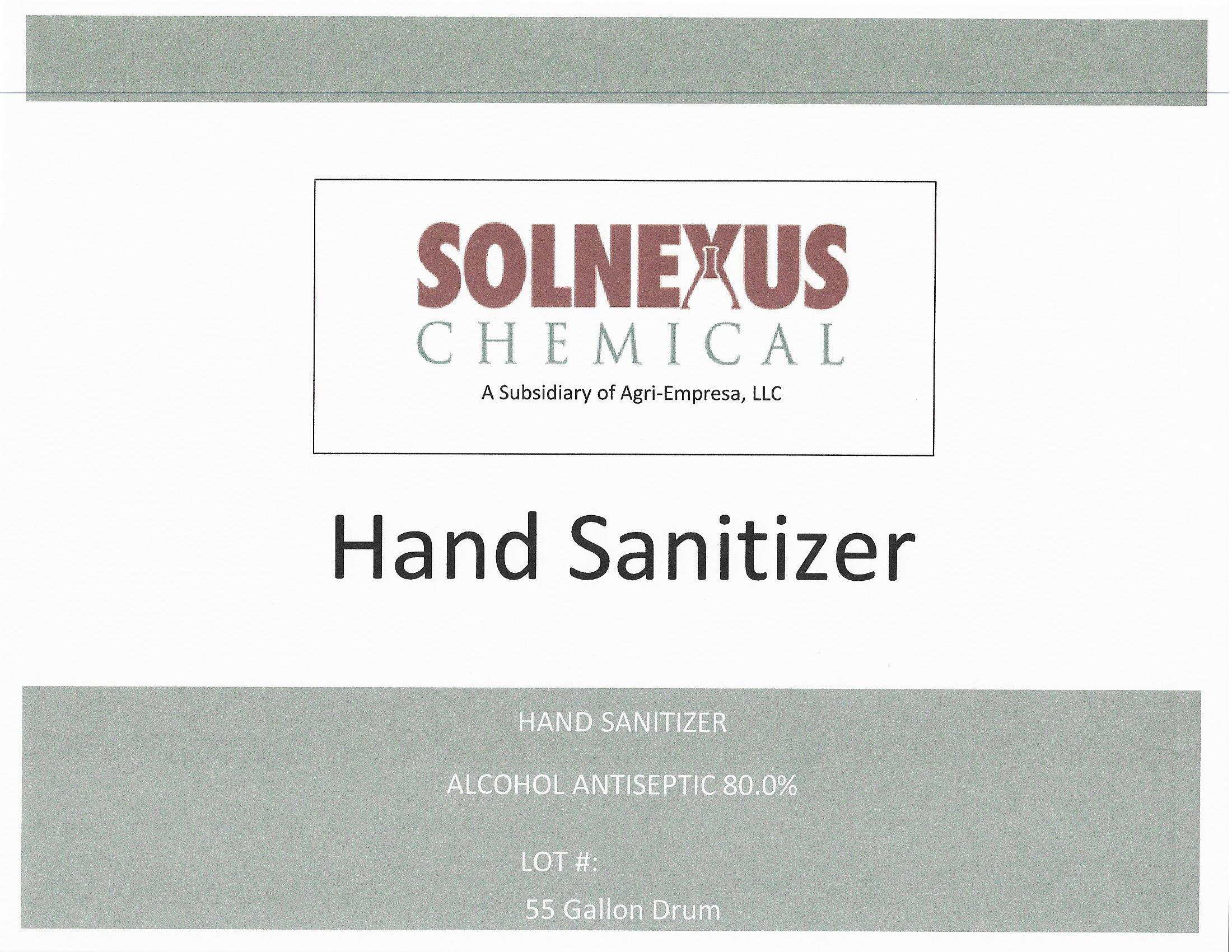 DRUG LABEL: Solnexus Chemical Hand Sanitizer
NDC: 76985-100 | Form: LIQUID
Manufacturer: Agri-Empresa
Category: otc | Type: HUMAN OTC DRUG LABEL
Date: 20200506

ACTIVE INGREDIENTS: ALCOHOL 80 mL/1000 mL
INACTIVE INGREDIENTS: HYDROGEN PEROXIDE 0.125 mL/1000 mL; GLYCERIN 1.45 mL/1000 mL; WATER 18.425 mL/1000 mL

Hand Sanitizer

Alcohol 80% v/v Purpose:Antiseptic

Alcohol 80% v/v Prpose: Antiseptic 33785.41 mL NDC 76985-100-01

Glycerin Water Hydrogen Peroxide

Solnexus 1 Gal Back

Indications and Usage

When using this product:

Keep out of eyes, ears, and mouth,

In case of contact with eyes, rinse thoroughly with water

Warnings

Flammable. Keep Away from Heat and Flame

Store Between 59-86 F

For External Use Only

Dosage & Administration

Can be Used On Hands and Surfaces

OTC-Keep Out of Reach of Children

If Swallowed, get Medical help Promply

Purpose

Antiseptic

Package Label

1.041 mL NDC 76985-100-04 208198 mL NDC 76985-100-03

Solnexus 55 Gal 18927.1 mL NDC 76985-100-02

Solnexus 5 Gal 3785.41 mL NDC76985-100-01

Solnexus 1 Gal